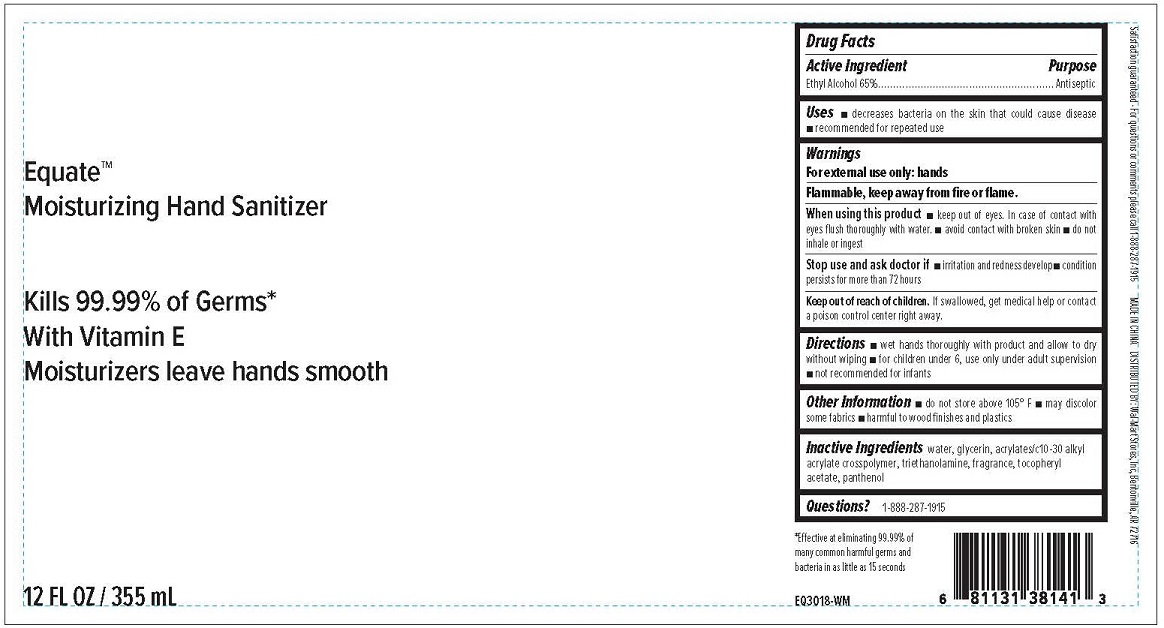 DRUG LABEL: EQUATE MOISTURIZING HAND SANITIZER WITH VITAMIN E
NDC: 49035-557 | Form: GEL
Manufacturer: Wal-Mart Stores, Inc.
Category: otc | Type: HUMAN OTC DRUG LABEL
Date: 20200407

ACTIVE INGREDIENTS: ALCOHOL 65 mL/100 mL
INACTIVE INGREDIENTS: WATER; GLYCERIN; CARBOMER INTERPOLYMER TYPE A (ALLYL SUCROSE CROSSLINKED); TROLAMINE; .ALPHA.-TOCOPHEROL ACETATE; PANTHENOL

EQUATE MOISTURIZING HAND SANITIZER WITH VITAMIN E

Active ingredient

ETHYL ALCOHOL 65%

Purpose

Antiseptic

Uses

- Decreases bacteria on the skin that could cause disease
- recommended for repeated use

WARNINGS

For external use only: hands
Flammable, keep away from fire or flame.
When using this product
• keep out of eyes. In case of contact with eyes flush thoroughly with water.
• avoid contact with broken skin
• do not inhale or ingest

Stop use and ask doctor if

- irritation and redness develop
- condition persists for more than 72 hours

Keep out of reach of children.

If swallowed, get medical hep or contact a Poison Control Center right away.

Directions

- wet hands thoroughly with product and allow to dry without wiping
- for children under 6, use only under adult supervision
- not recommended for infants

Other information

- not store above 105°F
- may discolor some fabrics
- harmful to wood finishes and plastics

Inactive ingredient

water, glycerin, acrylates/c10-30 alkyl acrylate crosspolymer, triethanolamine, fragrance, tocopheryl acetate, panthenol

Questions?

1-888-287-1915